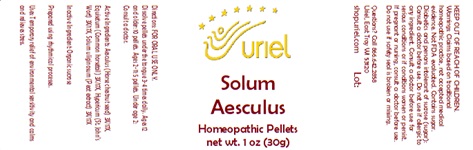 DRUG LABEL: Solum Aesculus
NDC: 48951-8319 | Form: PELLET
Manufacturer: Uriel Pharmacy Inc.
Category: homeopathic | Type: HUMAN OTC DRUG LABEL
Date: 20240809

ACTIVE INGREDIENTS: HORSE CHESTNUT 3 [hp_X]/1 1; EQUISETUM ARVENSE TOP 3 [hp_X]/1 1; ST. JOHN'S WORT 3 [hp_X]/1 1; SPHAGNUM SQUARROSUM PEAT 3 [hp_X]/1 1
INACTIVE INGREDIENTS: SUCROSE

Solum Aesculus

INDICATIONS AND USAGE

tions: FOR ORAL USE ONLY.

DOSAGE AND ADMINISTRATION

Dissolve pellets under the tongue 3-4 times daily. Ages 12 and older: 10 pellets. Ages 2-11: 5 pellets. Under age 2: Consult a doctor.

ACTIVE INGREDIENT

Active Ingredients: Aesculus (Horse chestnut seed) 3X/17X, Equisetum (Common horsetail) 3X/17X, Hypericum (St. John’s Wort) 3X/17X, Solum uliginosum (Peat extract) 3X/17X

Inactive Ingredient: Organic sucrose

Prepared using rhythmical processes.

PURPOSE

Uses: Temporary relief of environmental sensitivity and calms and relieves stress.

KEEP OUT OF REACH OF CHILDREN.

WARNINGS

Warnings: Claims based on traditional homeopathic practice, not accepted medical evidence. Not FDA evaluated. Contains sugar. Diabetics and persons intolerant of sucrose (sugar): Consult a doctor before use. Do not use if allergic to any ingredient. Consult a doctor before use for serious conditions or if conditions worsen or persist. If pregnant or nursing, consult a doctor before use. Do not use if safety seal is broken or missing.

Questions? Call 866.642.2858
Uriel, East Troy WI 53120
shopuriel.com